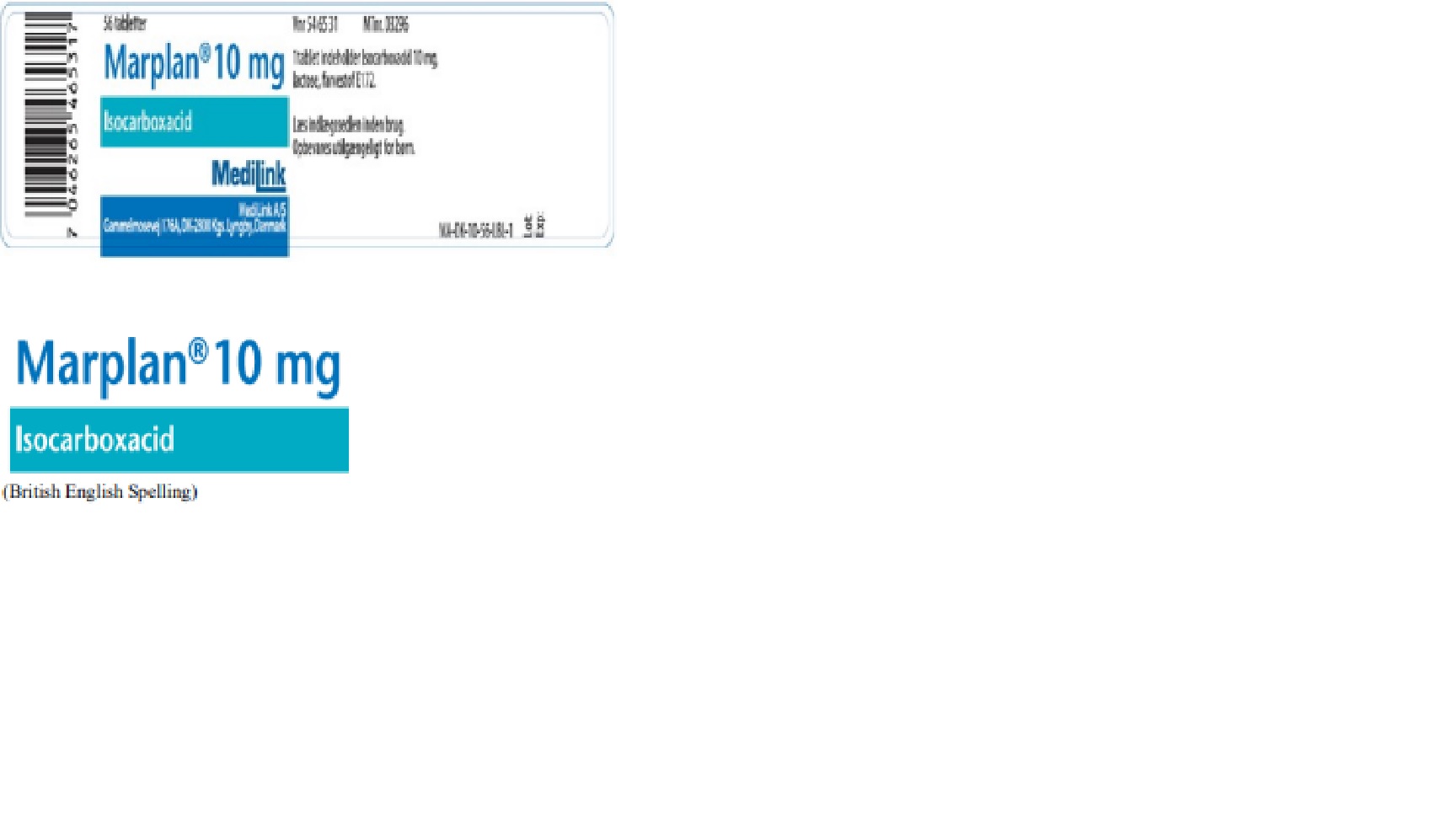 DRUG LABEL: Marplan
NDC: 72604-032 | Form: TABLET
Manufacturer: MediLink A/S
Category: prescription | Type: HUMAN PRESCRIPTION DRUG LABEL
Date: 20181220

ACTIVE INGREDIENTS: ISOCARBOXAZID 10 mg/1 1

Temporary Importation of Marplan (iscarboxacid) Tablets to Address Critical Drug Shortage

IMPORTANT PRESCRIBING INFORMATION

December 20, 2018

Subject: Temporary Importation of Marplan® (isocarboxacid) Tablets to Address Critical Drug Shortage

Dear Healthcare Professional,

In order to address the critical shortage of Marplan® (isocarboxazid) 10 mg Tablets in the United States (US) market, Validus Pharmaceuticals LLC is coordinating with the U.S. Food and Drug Administration (FDA) to make Marplan available to our patients. Validus has initiated temporary importation of another manufacturer’s Marplan (isocarboxacid) into the U.S. market. This product is manufactured and marketed in Denmark by MediLink.

At this time, no other entity except Validus Pharmaceuticals LLC is authorized by the FDA to import and distribute MediLink’s Marplan (isocarboxacid) 10 mg Tablets in the United States. FDA has not approved MediLink’s Marplan (isocarboxacid) 10 mg Tablets but does not object to its importation into the United States. Effective immediately, and during this temporary period, Validus will offer the following product:

Product Name and Description Bottle Count NDC Code Manufacturer Marplan (isocarboxacid) 10 mg Tablets 56 tablets 72604-032-01 MediLink

It is important to note the following:

• The labeling is in Danish. MediLink’s Marplan (isocarboxacid) 10 mg Tablets’ labeling, with the exception of the product name “Marplan”, will appear in Danish. There are key differences in the labeling between Validus’ Marplan and Medilink’s Marplan. A side by side comparison of the FDA approved Marplan (isocarboxazid) Prescribing Information and the imported Marplan (isocarboxacid) product information is included at the end of this letter.

• The tablets have different appearance. MediLink’s Marplan (isocarboxacid) 10 mg tablets are “dull pink” in color whereas Validus’ Marplan (isocarboxazid) 10 mg tablets are “peach-colored.” MediLink’s Marplan 10 mg tablets are imprinted with “CL 3M3” whereas Validus’ Marplan 10 mg tablets are imprinted with “Marplan” and “10” on one side. Please refer to the “Product Comparison” table at the end of this letter for details and images.

• The barcode may not register accurately in the U.S. scanning systems. Institutions should manually input the product into their systems and confirm that the barcode Marplan DHCP Letter Page 1 of 22 systems do not provide incorrect information when the product is scanned. Alternative procedures should be followed to assure that the correct drug product is being used and administered to individual patients.

To order, or if you have any questions about MediLink’s Marplan, please contact Validus Customer Service by phone at 1-866-982-5438 or by e-mail at info@validuspharma.com.

To report Adverse Events or Quality Problems among patients who have received - MediLink’s Marplan, please contact Validus at 1-866-982-5438 or by e-mail at info@validuspharma.com. Adverse events or quality problems may also be reported to FDA’s MedWatch Adverse reporting Program either online, by regular mail, or by fax:

• Complete and submit the report Online: www.fda.gov/medwatch/report.htm

• Regular Mail or Fax: Download form www.fda.gov/Medwatch/getforms.htm or call 1- 800-332-1088 to request a reporting form. Complete and return the form to the address on the pre-addressed form, or submit it by fax to 1-800-FDA-0178 (1-800- 332-1078).

If you have any questions about the information contained in this letter or the safe and effective use of MediLink’s Marplan (isocarboxacid) 10mg Tablets, please contact Validus at 1-866-982- 5438 or by e-mail at info@validuspharma.com.

Sincerely,

Gina Walljasper

Sr. Director Regulatory and Quality Operations

Validus Pharmaceuticals LLC

Principal Display Panel - Marplan (isocarboxacid) 10mg Tablets

Marplan 10 mg is a round and flat, pink tablet with a break line on one side and labeled CL 3M3 on the other side.